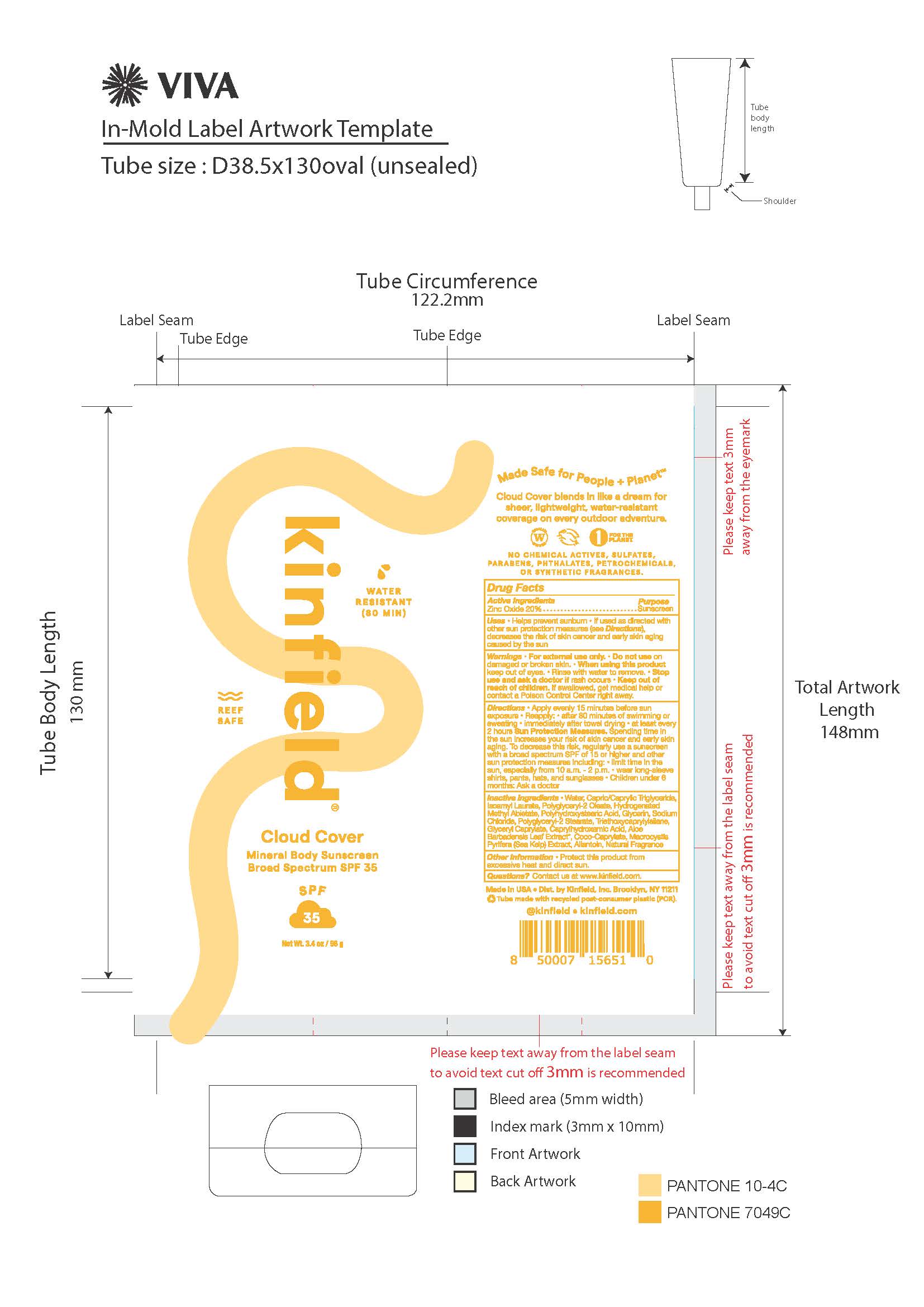 DRUG LABEL: Kinfield Cloud Cover Mineral Body Sunscreen Broad Spectrum SPF 35
NDC: 81750-041 | Form: LOTION
Manufacturer: Kinfield, Inc.
Category: otc | Type: HUMAN OTC DRUG LABEL
Date: 20251230

ACTIVE INGREDIENTS: ZINC OXIDE 20 g/100 g
INACTIVE INGREDIENTS: WATER; CAPRYLIC/CAPRIC/LAURIC TRIGLYCERIDE; ISOAMYL LAURATE; POLYGLYCERYL-2 OLEATE; HYDROGENATED METHYL ABIETATE; POLYHYDROXYSTEARIC ACID (2300 MW); GLYCINE; SODIUM CHLORIDE; POLYGLYCERYL-2 STEARATE; TRIETHOXYCAPRYLYLSILANE; GLYCERYL CAPRATE; CAPRYLHYDROXAMIC ACID; ALOE VERA LEAF; COCO-CAPRYLATE; MACROCYSTIS PYRIFERA; ALLANTOIN

DRUG FACTS

Active Ingredients

Zinc Oxide 20%

Uses

• helps prevent sunburn • if used as directed with other
sun protection measures (see Directions), decreases the
risk of skin cancer and early skin aging caused by the sun

Warnings

For external use only
Do not use on damaged or broken skin.
When using this product keep out of eyes. Rinse with water to remove.
Stop use and ask a docor if rash occurs
Keep out of reach of children. If swalled, get medical help or contact a Poison Control Center right away.

Directions

• apply liberally 15 minutes before sun exposure
• reapply:
• after 80 minutes of swimming or sweating
• immediately after towel drying
• at least every 2 hours
• Sun Protection Measures. Spending time in the sun increases your risk
of skin cancer and early skin aging. To decrease this risk, regularly use
a sunscreen with a broad spectrum SPF of 15 or higher and other sun
protection measures including:
• limit time in the sun, especially from 10 a.m. – 2 p.m.
• wear long-sleeve shirts, pants, hats, and sunglasses
• children under 6 months: Ask a doctor

Inactive ingredients

Water, Capric/Caprylic Triglyceride, Isoamyl Laurate, Polyglyceryl-2 Oleate, Hydrogenated Methyl Abietate, Polyhydrostearic Acide, Glycerin, Sodium Chloride, Polyglyceryl-2 Stearate, Triethoxycaprylylsilane, Glyceryl Caprylate, Caprylhydroxamic Acid, Aloe Barbadnesis Leaf Extract, Coco-Caprylate, Macrocystis Pyrifera (Sea Kelp) Extract, Allantoin, Natural Fragrance

Other Information

• protect the product in this container from excessive
heat and direct sun

Questions or Comments?

Conctact us at www.kinfield.com

Keep out of reach of children. If product is swallowed, get medical help or contact a Poison Control Center right away.

Purpose

Purpose: Sunscreen